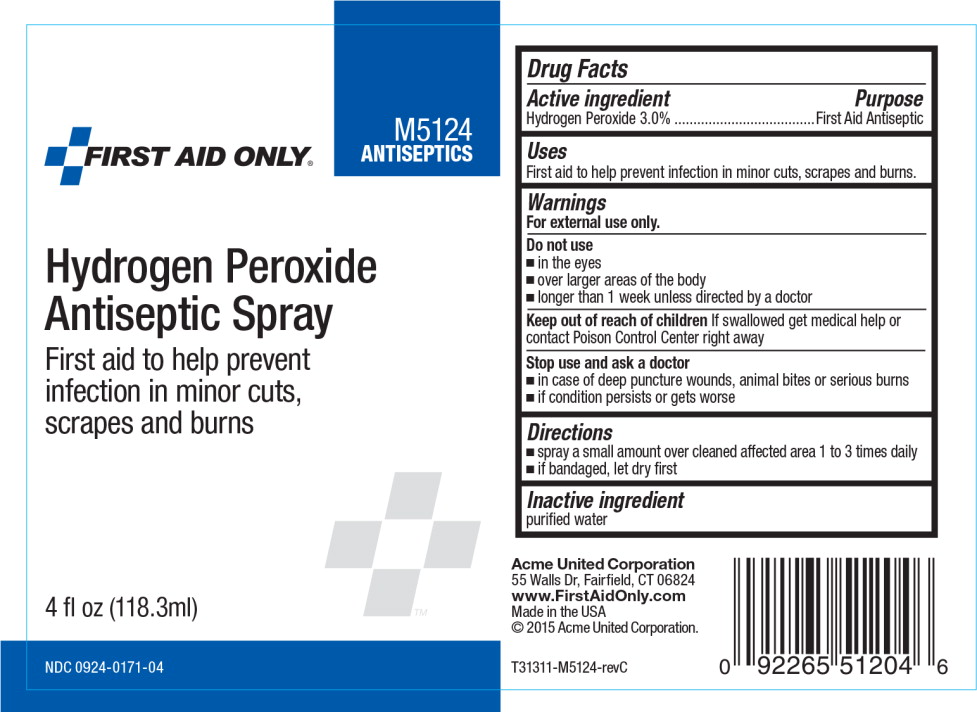 DRUG LABEL: First Aid Only Hydrogen Peroxide

NDC: 0924-0171 | Form: SPRAY
Manufacturer: Acme United Corp.

Category: otc | Type: HUMAN OTC DRUG LABEL
Date: 20160223

ACTIVE INGREDIENTS: Hydrogen Peroxide
 30 mL/1 L
INACTIVE INGREDIENTS: water

Drug Facts

Active ingredient

Hydrogen Peroxide 3.0%

Purpose

First Aid Antiseptic

Uses

First aid to help prevent infection in minor cuts, scrapes and burns.

Warnings

For external use only

Do not use

- in the eyes
- over larger areas of the body
- longer than 1 week unless directed by a doctor

Keep out of reach of children If swallowed get medical help or contact Poison Control Center right away

Stop use and ask a doctor

- in case of deep puncture wounds, animal bites, or serious burns
- if condition persists or gets worse

Directions

- spray a small amount over cleaned affected area 1 to 3 times daily
- if bandaged, let dry first

Inactive ingredient

purified water

Principal Display Panel - Bottle Label

FIRST AID ONLY®

M5124

ANTISEPTICS

Hydrogen Peroxide
Antiseptic Spray

First aid to help prevent
infection in minor cuts,
scrapes and burns

4 fl oz (118.3ml)

NDC 0924-0171-04